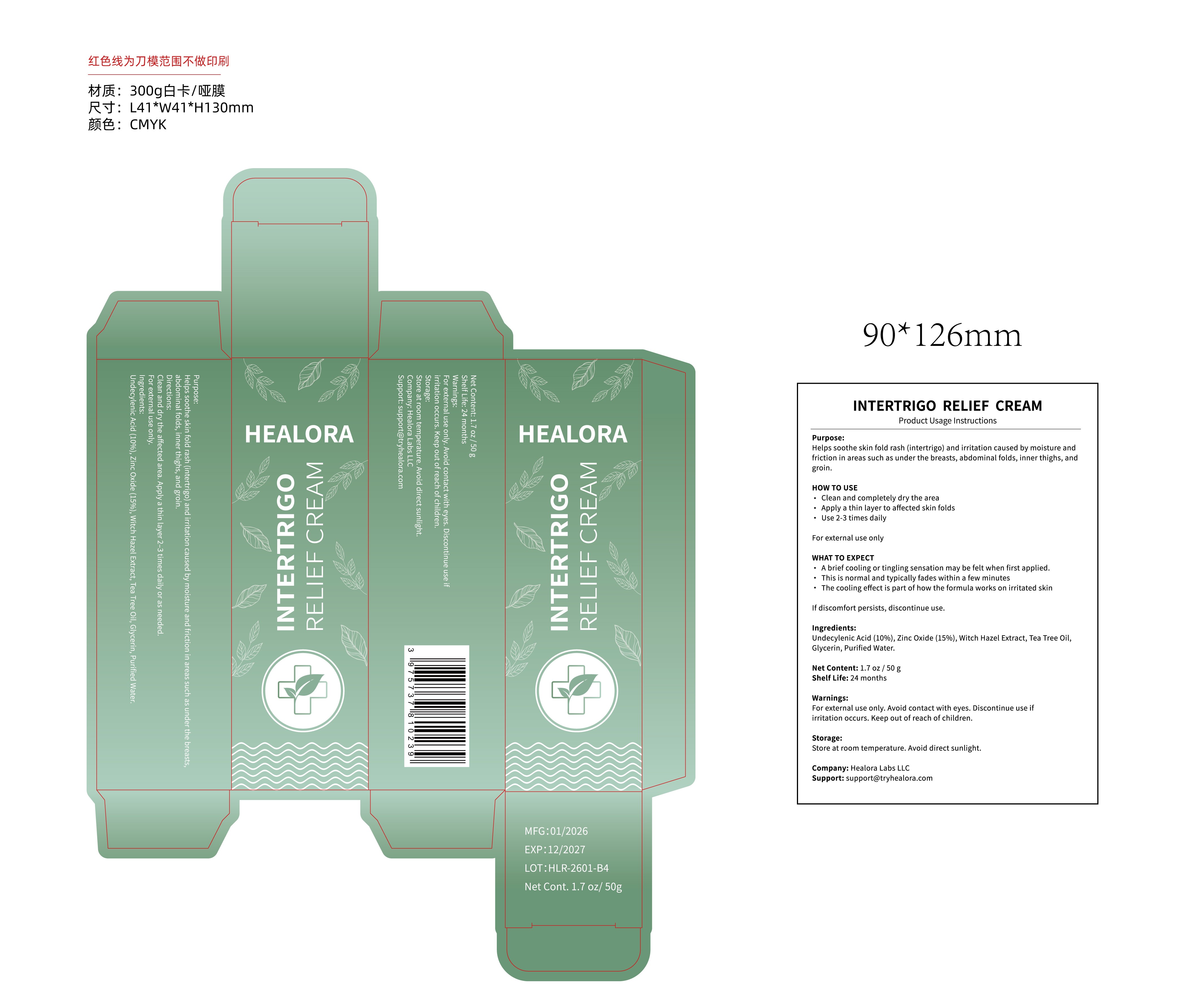 DRUG LABEL: INTERTRIGO RELIEF
NDC: 85593-030 | Form: CREAM
Manufacturer: Guangzhou ChuanMa International Trading Co.,Ltd.
Category: otc | Type: HUMAN OTC DRUG LABEL
Date: 20260126

ACTIVE INGREDIENTS: ZINC OXIDE 15 g/100 g; UNDECYLENIC ACID 10 g/100 g
INACTIVE INGREDIENTS: TEA TREE OIL; GLYCERIN; WITCH HAZEL; WATER

ACTIVE INGREDIENT

Undecylenic Acid (10%), Zinc Oxide (15%)

PURPOSE

Helps soothe skin fold rash (intertrigo) and irritation caused by moisture and friction in areas such as under the breasts, abdominal folds, inner thighs, andgroin.

Keep out of reach of children

DOSAGE AND ADMINISTRATION

Use 2-3 times daily

WARNINGS

Warnings:For external use only. Avoid contact with eyes. Discontinue use ifirritation occurs. Keep out of reach of children.

INDICATIONS AND USAGE

A brief cooling or tingling sensation may be felt when first applied.. This is normal and typically fades within a few minutes. The cooling effect is part of how the formula works on irritated skin

INACTIVE INGREDIENT

Witch Hazel Extract, Tea Tree Oil,Glycerin, Purified Water.